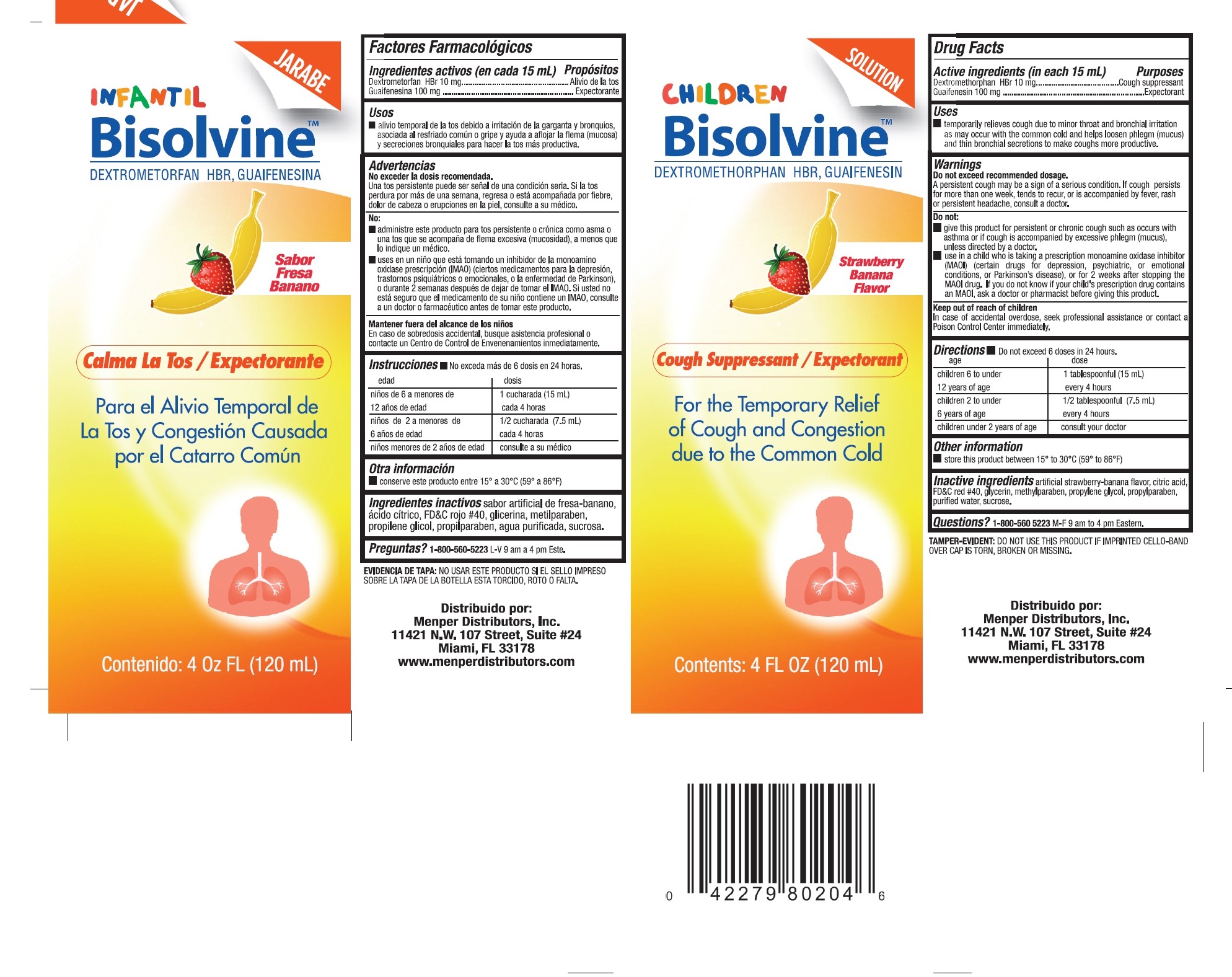 DRUG LABEL: Bisolvine
NDC: 53145-322 | Form: LIQUID
Manufacturer: MENPER DISTRIBUTORS INC.
Category: otc | Type: HUMAN OTC DRUG LABEL
Date: 20250722

ACTIVE INGREDIENTS: GUAIFENESIN 100 mg/15 mL; DEXTROMETHORPHAN HYDROBROMIDE 10 mg/15 mL
INACTIVE INGREDIENTS: FD&C RED NO. 40; GLYCERIN; METHYLPARABEN; PROPYLENE GLYCOL; PROPYLPARABEN; WATER; SUCROSE; CITRIC ACID MONOHYDRATE

Bisolvine Children

Active Ingredients (in each 15 mL)

Guaifenesin 100 mg ................................................ Expectorant

Dextromethorphan.............................................. Cough Suppressant

Purpose

Expectorant

Cough Suppressant

Uses

temporarily relieves cough due to minor throat and bronchial irritation as may occur with the common cold and helps loosen phlegm (mucus) and thin bronchial secretions to make coughs more productive.

Warnings:

Do not exceed recommended dosage.

A persistent cough may be a sign of a serious condition. If cough persists for more than one week, tends to recur, or is accompanied by fever, rash, or persistent headache, consult a doctor.

Do not:

- give this product for persistent or chronic cough, such as occurs with asthma, or emphysema or if cough is accompanied by excessive phlegm (mucus), unless directed by a doctor.
- use in a child who is taking a prescription monoamine oxidase inhibitor (MAOI) (certain drugs for depression, psychiatric, or emotional conditions, or Parkinson's Disease), or for 2 weeks after stopping the MAOI drug. If you do not know if your child's prescription drug contains an MAOI, ask a doctor or pharmacist before giving this product.

Keep out of reach of children

In case of accidental overdose, seek professional assisstance or contact a Poison Control Center immediately.

Directions

Age | Dose
Children 6 to under 12 years of age | 1 teaspoonful (15 mL) every 4 hours
Children 2 to under 6 years of age | 1/2 teaspoonful (7.5 mL) every 4 hours
Children under 2 years of age | Consult your doctor

OTHER SAFETY INFORMATION

store this product between 15° to 30° C (59°-86° F)

INACTIVE INGREDIENT

artificial strawberryt-banana flavor, citric acid, fd&c red #40, glycerin, methylparaben, propylene glycol, propylparaben, puridied water, sucrose.

Questions?

1-800-560-5223 M-F 9 AM to 4 PM Eastern.